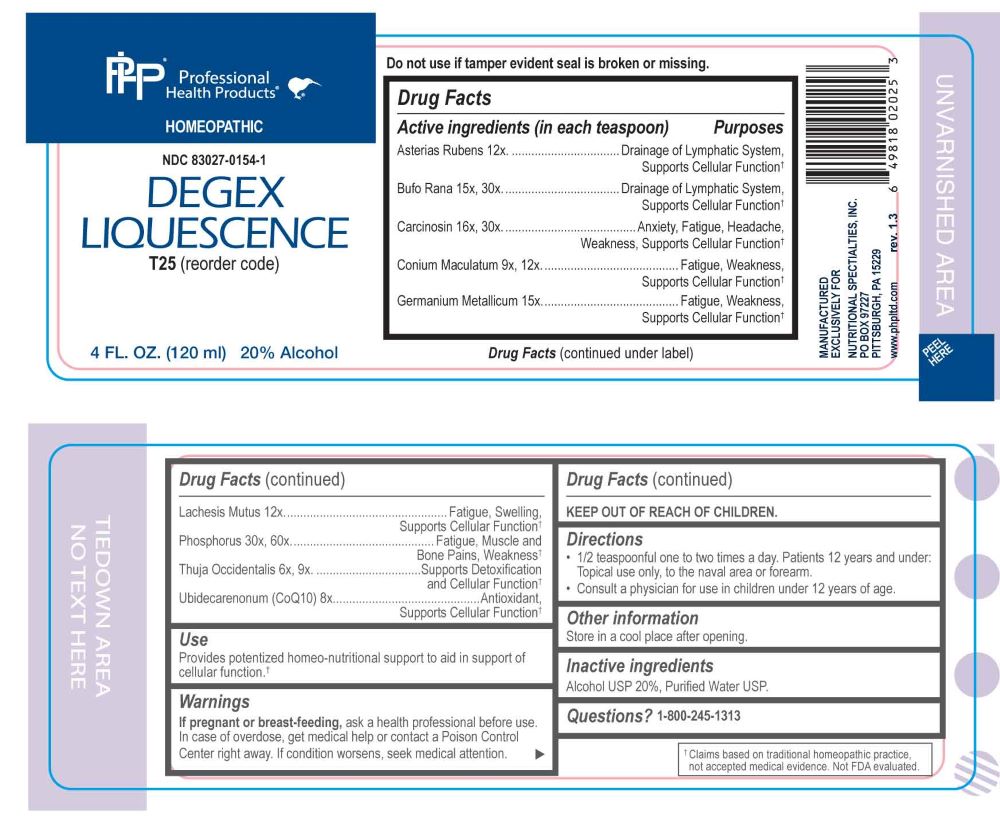 DRUG LABEL: Degex Liquescence
NDC: 83027-0154 | Form: LIQUID
Manufacturer: Nutritional Specialties, Inc.
Category: homeopathic | Type: HUMAN OTC DRUG LABEL
Date: 20250923

ACTIVE INGREDIENTS: THUJA OCCIDENTALIS LEAFY TWIG 6 [hp_X]/1 mL; UBIDECARENONE 8 [hp_X]/1 mL; CONIUM MACULATUM FLOWERING TOP 9 [hp_X]/1 mL; ASTERIAS RUBENS 12 [hp_X]/1 mL; GERMANIUM 15 [hp_X]/1 mL; LACHESIS MUTA VENOM 12 [hp_X]/1 mL; BUFO BUFO CUTANEOUS GLAND 15 [hp_X]/1 mL; HUMAN BREAST TUMOR CELL 16 [hp_X]/1 mL; PHOSPHORUS 30 [hp_X]/1 mL
INACTIVE INGREDIENTS: WATER; ALCOHOL

DRUG FACTS:

ACTIVE INGREDIENTS:

Asterias Rubens 12X, Bufo Rana 15X, 30X, Carcinosin 16X, 30X, Conium Maculatum 9X, 12X, Germanium Metallicum 15X, Lachesis Mutus 12X, Phosphorus 30X, 60X, Thuja Occidentalis 6X, 9X, Ubidecarenonum 8X.

PURPOSE:

Asterias Rubens – Drainage of Lymphatic System, Supports Cellular Function,† Bufo Rana - Drainage of Lymphatic System, Supports Cellular Function,† Carcinosin – Anxiety, Fatigue, Headache, Weakness, Supports Cellular Function,† Conium Maculatum – Fatigue, Weakness, Supports Cellular Function,† Germanium Metallicum - Fatigue, Weakness, Supports Cellular Function,† Lachesis Mutus – Fatigue, Swelling, Supports Cellular Function,† Phosphorus – Fatigue, Muscle and Bone Pains, Weakness,† Thuja Occidentalis – Supports Detoxification and Cellular Function,† Ubidecarenonum – Antioxidant, Supports Cellular Function†

†Claims based on traditional homeopathic practice, not accepted medical evidence. Not FDA evaluated.

USES:

Provides potentized homeo-nutritional support to aid in support of cellular function.†

†Claims based on traditional homeopathic practice, not accepted medical evidence. Not FDA evaluated.

WARNINGS:

If pregnant or breast-feeding, ask a health professional before use.

In case of overdose, get medical help or contact a Poison Control Center right away.

If condition worsens, seek medical attention.

KEEP OUT OF REACH OF CHILDREN

Do not use if tamper evident seal is broken or missing.

Store in a cool place after opening

KEEP OUT OF REACH OF CHILDREN:

In case of overdose, get medical help or contact a Poison Control Center right away.

DIRECTIONS:

• 1/2 teaspoonful one to two times a day. Patients 12 years and under, Topical use only, to the naval area or forearm.

• Consult a physician for use in children under 12 years of age.

INACTIVE INGREDIENTS:

Alcohol USP 20%, Purified Water USP.

QUESTIONS:

MANUFACTURED EXCLUSIVELY FOR

NUTRITIONAL SPECIALTIES, INC.

PO BOX 97227

PITTSBURGH, PA 15229

www.phpitd.com

1-800-245-1313

PACKAGE LABEL DISPLAY:

Professional Health Products

HOMEOPATHIC

NDC 83027-0154-1

DEGEX LIQUESCENCE

4 FL. OZ. (120ml)